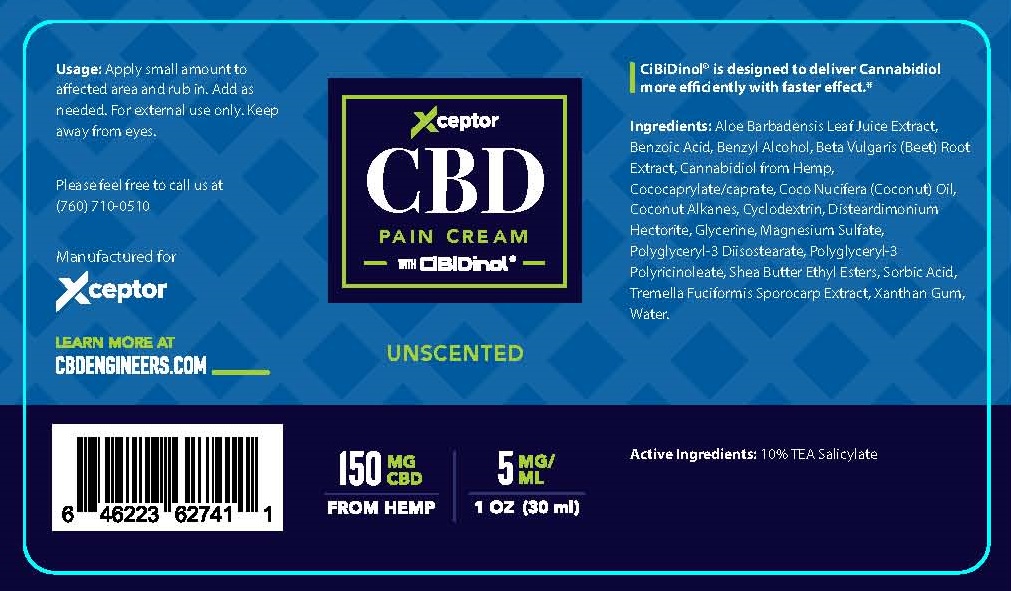 DRUG LABEL: XCEPTOR CBD PAIN
NDC: 72519-102 | Form: CREAM
Manufacturer: XCEPTOR LLC
Category: otc | Type: HUMAN OTC DRUG LABEL
Date: 20200901

ACTIVE INGREDIENTS: TROLAMINE SALICYLATE 10 g/100 mL
INACTIVE INGREDIENTS: ALOE VERA LEAF; BENZOIC ACID; BENZYL ALCOHOL; BEET; CANNABIDIOL; COCO-CAPRYLATE/CAPRATE; COCONUT OIL; COCONUT ALKANES; BETADEX; DISTEARDIMONIUM HECTORITE; GLYCERIN; MAGNESIUM SULFATE ANHYDROUS; POLYGLYCERYL-3 DIISOSTEARATE; POLYGLYCERYL-3 RICINOLEATE; SHEA BUTTER ETHYL ESTERS; SORBIC ACID; TREMELLA FUCIFORMIS FRUITING BODY; WATER; XANTHAN GUM

XCEPTOR CBD PAIN CREAM - UNSCENTED

ACTIVE INGREDIENTS

TEA SALICYLATE 10%

PURPOSE

TOPICAL ANALGESIC

USES

TOPICAL PAIN RELIEF FOR MINOR ACHES AND PAINS.

WARNINGS

FOR EXTERNAL USE ONLY.

KEEP AWAY FROM EYES.

KEEP OUT OF REACH OF CHILDREN.

DIRECTIONS

APPLY SMALL AMOUNT TO AFFECTED AREA AND RUB IN. ADD AS NEEDED.

OTHER INFORMATION

STORE AT 20° - 25°C (68°-77°F)

INACTIVE INGREDIENTS

ALOE BARBADENSIS LEAF JUICE EXTRACT, BENZOIC ACID, BENZYL ALCOHOL, BETA VULGARIS (BEET) ROOT EXTRACT, CANNABIDIOL FROM HEMP, COCOCAPRYLATE/CAPRATE, COCOS NUCIFERA (COCONUT) OIL, COCONUT ALKANES, CYCLODEXTRIN, DISTEARDIMONIUM HECTORITE, GLYCERIN, MAGNESIUM SULFATE, POLYGLYCERYL-3 DIISOSTEARATE, POLYGLYCERYL-3 POLYRICINOLEATE, SHEA BUTTER ETHYL ESTERS, SORBIC ACID, TREMELLA FUCIFORMIS SPOROCARP EXTRACT, XANTHAN GUM, WATER

QUESTIONS / COMMENTS?

PLEASE CALL US AT (760) 710-0510